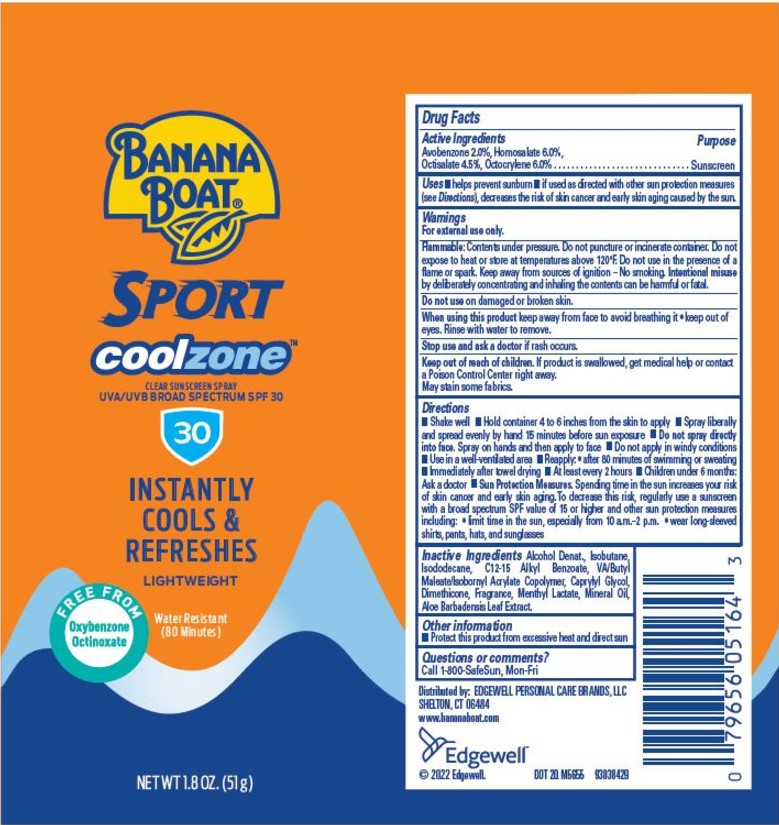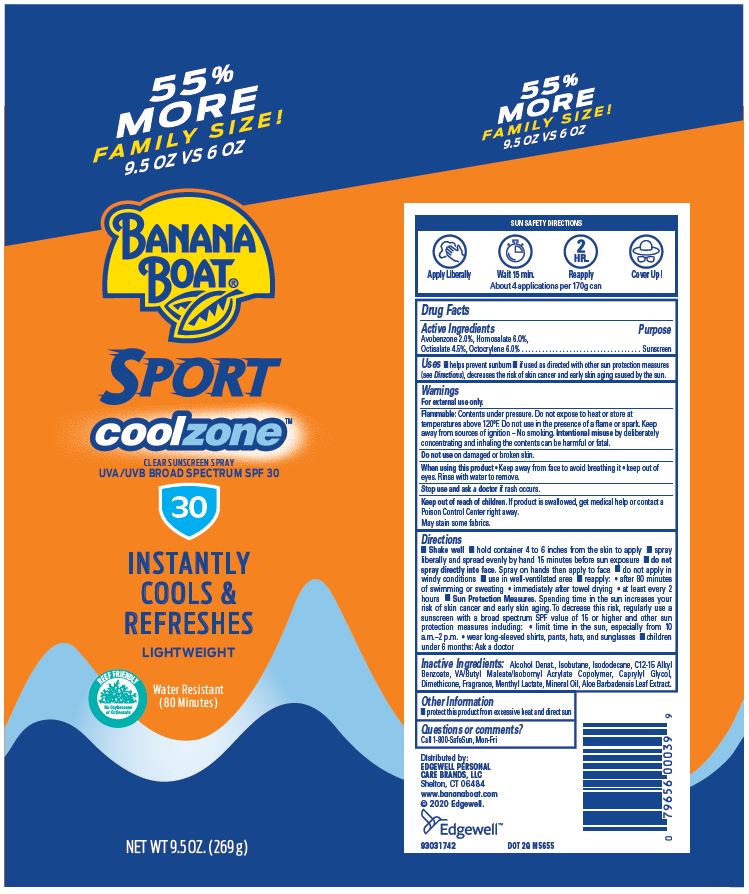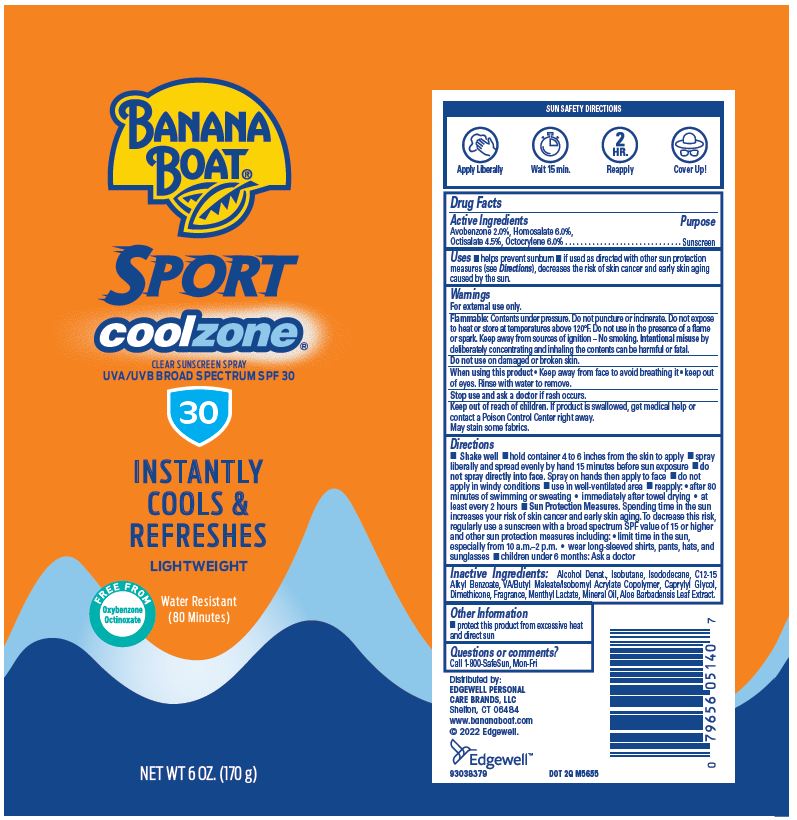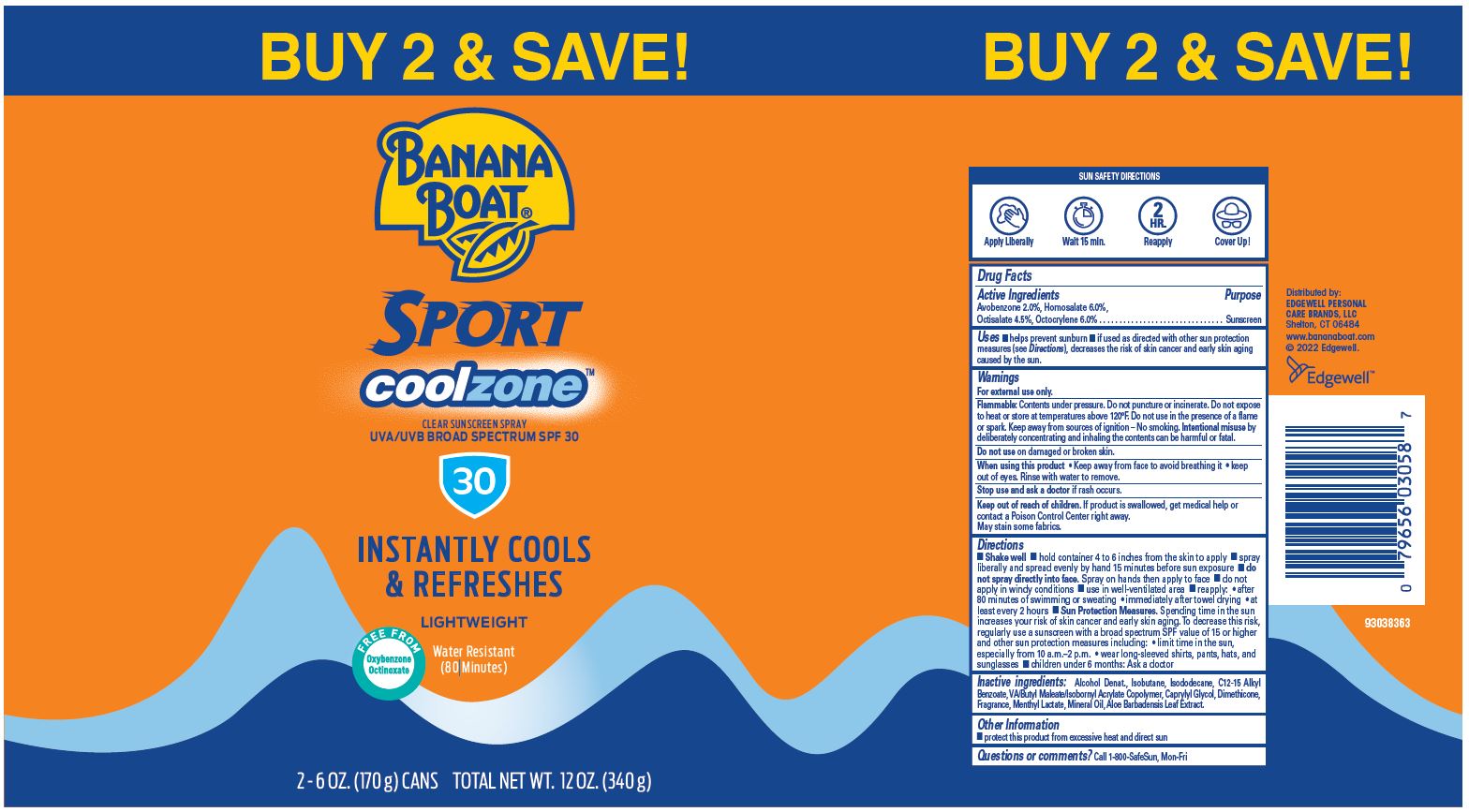 DRUG LABEL: Banana Boat Sport coolzone Clear Sunscreen Broad Spectrum SPF 30
NDC: 63354-211 | Form: SPRAY
Manufacturer: Edgewell Personal Care Brands LLC
Category: otc | Type: HUMAN OTC DRUG LABEL
Date: 20251106

ACTIVE INGREDIENTS: HOMOSALATE 6 g/100 g; AVOBENZONE 2 g/100 g; OCTOCRYLENE 6 g/100 g; OCTISALATE 4.5 g/100 g
INACTIVE INGREDIENTS: MENTHYL LACTATE, (-)-; ALOE VERA LEAF; ALCOHOL; ISOBUTANE; CAPRYLYL GLYCOL; ALKYL (C12-15) BENZOATE; MINERAL OIL; ISODODECANE; DIMETHICONE

ACTIVE INGREDIENTS

Avobenzone 2.0%, Homosalate 6.0%, Octisalate 4.5%, Octocrylene 6.0%

Purpose

Sunscreen

Uses

• helps prevent sunburn • if used as directed with other sun protection measures (see Directions), decreases the risk of skin cancer and early skin aging caused by the sun

Warnings

For external use only.

Flammable: Contents under pressure. Do not puncture or incinerate. Do not expose to heat or store at temperatures above 120°F. Do not use in the presense of a flame or spark. Keep away from sources of ignition - No smoking. Intentional misuse by deliberately concentrating and inhaling the contents can be harmful or fatal

May stain some fabrics.

Do not use

on damaged or broken skin

When using this product

• Keep away from face to avoid breathing it • keep out of eyes. Rinse with water to remove.

Stop use and ask a doctor

if rash occurs

Keep out of reach of children

If product is swallowed, get medical help or contact a Poison Control Center right away.

Directions

• Shake Well • Hold container 4 to 6 inches from the skin to apply • spray liberally and spread evenly by hand 15 minutes before sun exposure • do not spray directly into face. Spray on hands then apply to face. • do not apply in windy conditions • Use in well-ventilated area • Reapply: • after 80 minutes of swimming or sweating • immediately after towel drying • at least every 2 hours • Sun Protection Measures. Spending time in the sun increases your risk of skin cancer and early skin aging. To decrease this risk, regularly use a sunscreen with a broad spectrum SPF value of 15 or higher and other sun protection measures including: • limit time in the sun, especially from 10 a.m. - 2 p.m. • wear long-sleeved shirts, pants, hats, and sunglasses • children under 6 months: Ask a doctor

Inactive Ingredients

Alcohol Denat., Isobutane, Isododecane, C12-15 Alkyl Benzoate, VA/Butyl Maleate/Isobornyl Acrylate Copolymer, Caprylyl Glycol, Dimethicone, Fragrance, Menthyl Lactate, Mineral Oil, Aloe Barbadensis Leaf Extract

Other information

• protect this product from excessive heat and direct sun

Questions or comments?

Call 1-800-SafeSun, Mon-Fri

Primary Display Panel

BANANA

BOAT®
SPORT
coolzone
CLEAR SUNSCREEN SPRAY
UVA/UVB BROAD SPECTRUM SPF 30
30
INSTANTLY
COOLS &
REFRESHES
LIGHTWEIGHT
FREE FROM
Oxybenzone
Octinoxate
Water Resistant
(80 Minutes)
NET WT 6 OZ. (170 g)

55%
MORE
FAMILY SIZE!
9.5 OZ VS 6 OZ
BANANA
BOAT®
SPORT
coolzone
CLEAR SUNSCREEN SPRAY
UVA/UVB BROAD SPECTRUM SPF 30
30
INSTANTLY
COOLS &
REFRESHES
LIGHTWEIGHT
REEF FRIENDLY
No Oxybenzone
or Octinoxate
Water Resistant
(80 Minutes)
NET WT 9.5 OZ. (269 g)

BUY 2 & SAVE!
BANANA
BOAT®
SPORT
coolzone
CLEAR SUNSCREEN SPRAY
UVA/UVB BROAD SPECTRUM SPF 30
30
INSTANTLY
COOLS &
REFRESHES
LIGHTWEIGHT
FREE FROM
Oxybenzone
Octinoxate
Water Resistant
(80 Minutes)
2 - 6 OZ. (170 g) CANS TOTAL NET WT. 12 OZ. (340 g)

BANANA
BOAT®
SPORT
coolzone
CLEAR SUNSCREEN SPRAY
UVA/UVB BROAD SPECTRUM SPF 30
30
INSTANTLY
COOLS &
REFRESHES
LIGHTWEIGHT
FREE FROM
Oxybenzone
Octinoxate
Water Resistant
(80 Minutes)
NET WT 1.8 OZ. (51g)